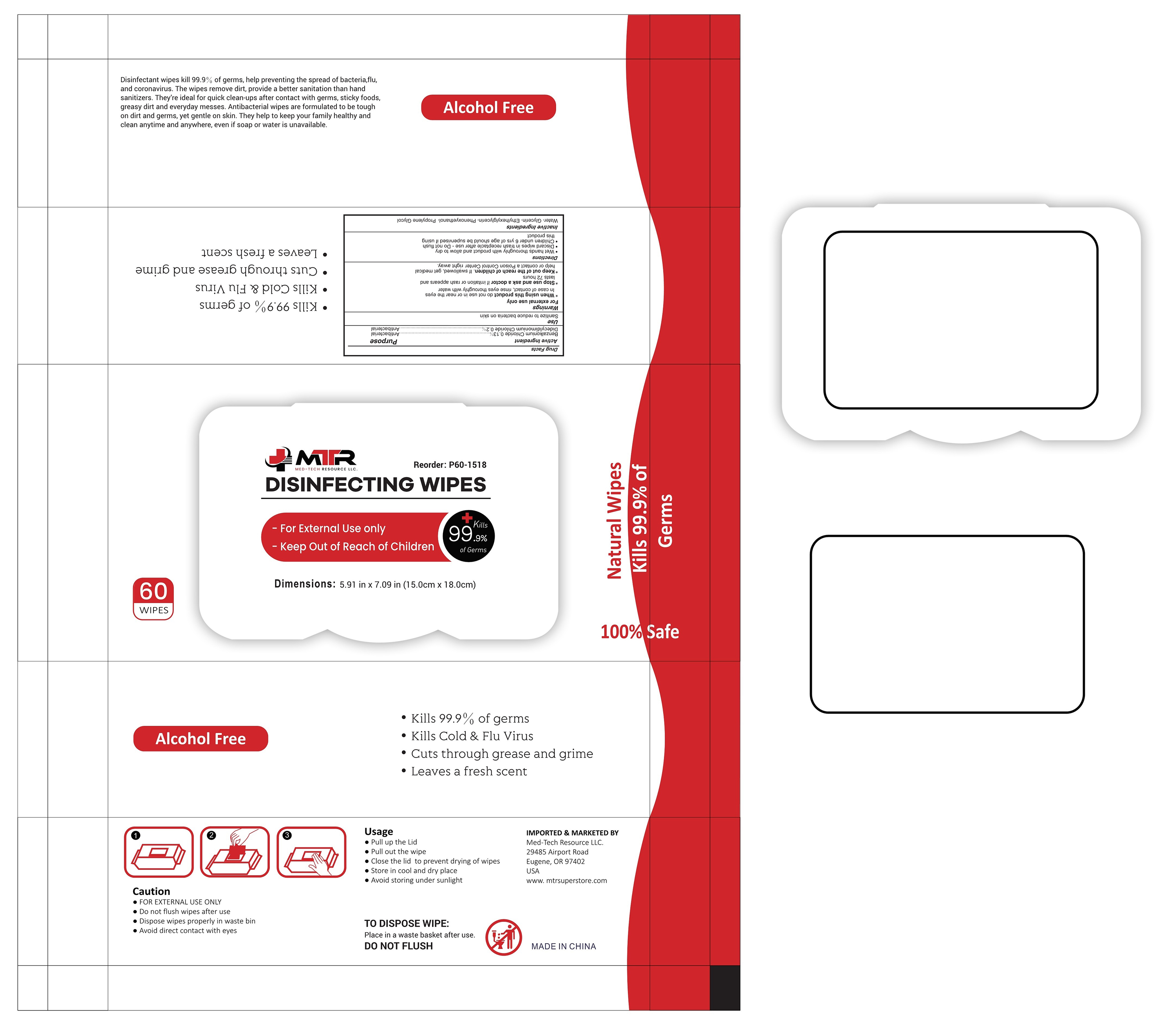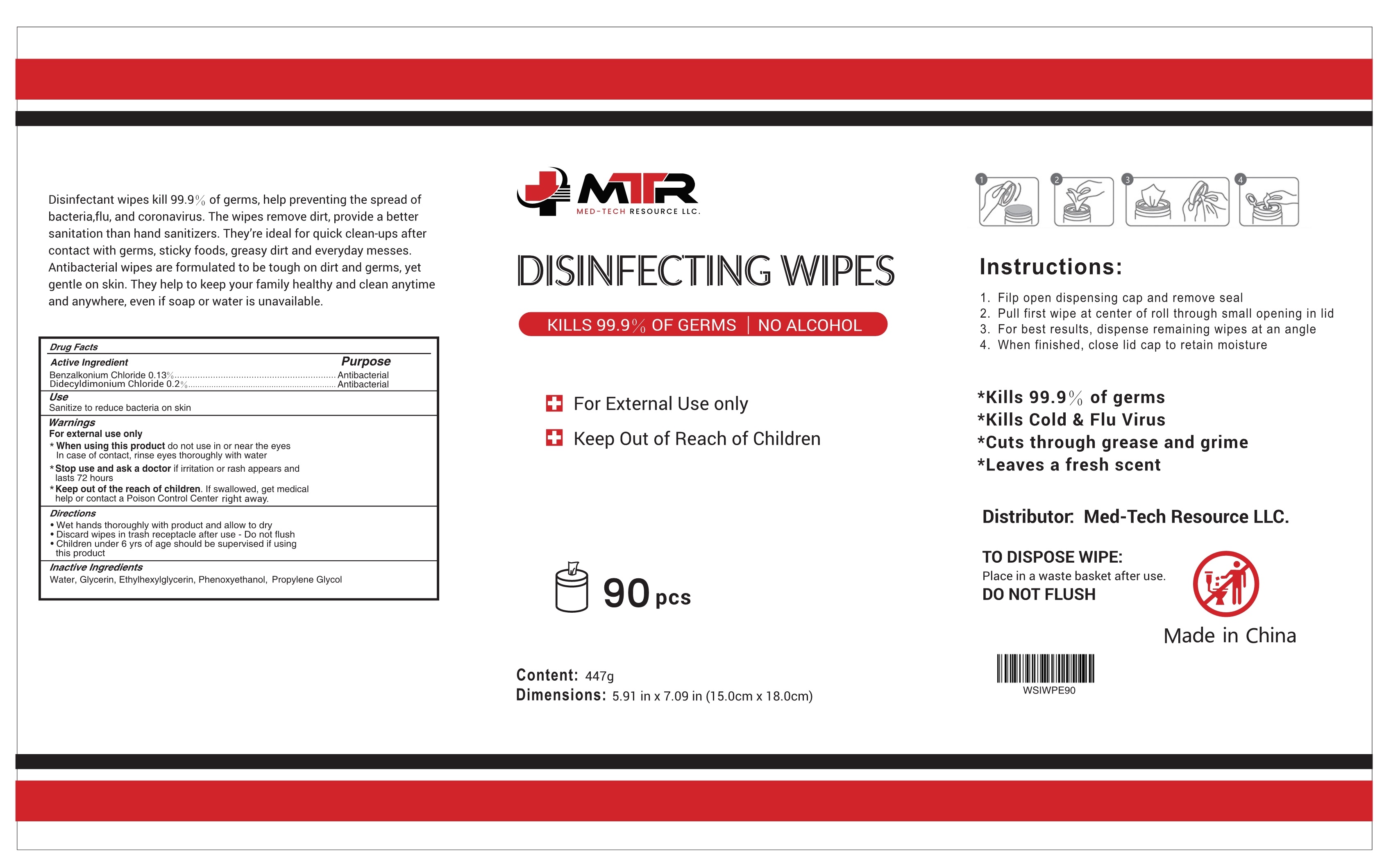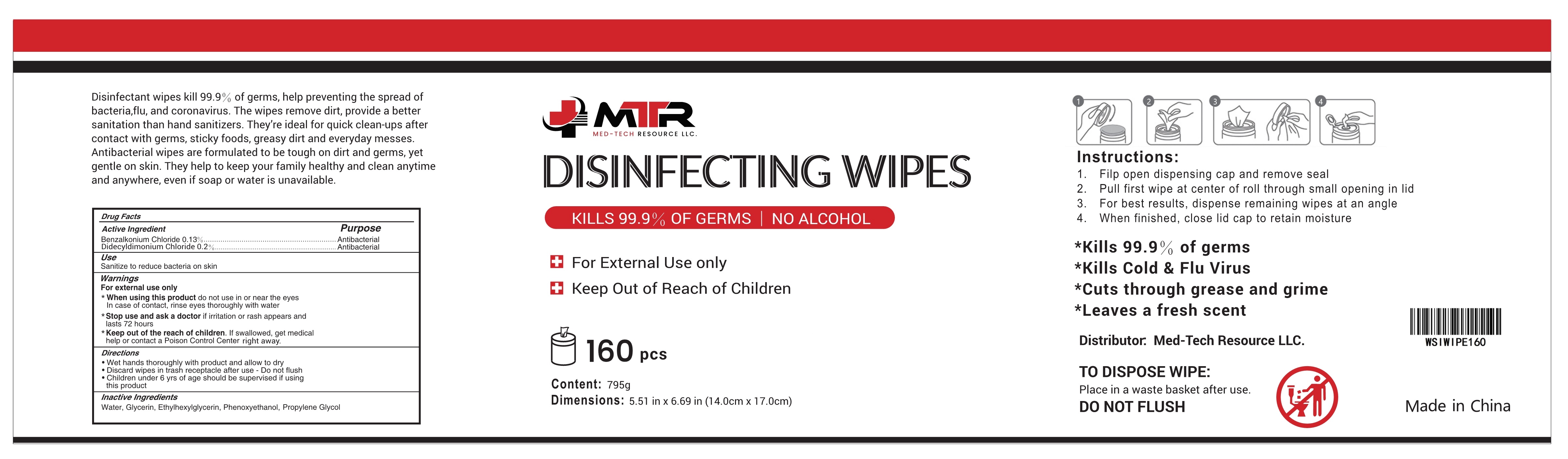 DRUG LABEL: DISINFECTING WIPES
NDC: 79683-005 | Form: CLOTH
Manufacturer: Hefei Inridy Medical Products Co., Ltd
Category: otc | Type: HUMAN OTC DRUG LABEL
Date: 20210416

ACTIVE INGREDIENTS: BENZALKONIUM CHLORIDE 0.13 g/100 1; DIDECYLDIMONIUM CHLORIDE 0.2 g/100 1
INACTIVE INGREDIENTS: WATER; PHENOXYETHANOL; ETHYLHEXYLGLYCERIN; PROPYLENE GLYCOL DIBUTYRATE; GLYCERIN

79683-005
DISINFECTING WIPES

Active Ingredient(s)

Benzalkonium Chloride 0.13%..........Antibacterial
Didecyldimonium Chloride 0.2%..........Antibacterial

Purpose

Antibacterial

Use

Sanitize to reduce bacteria on skin

Warnings

For external use only
*When using this product do not use in or near the eyes
In case of contact, rinse eyes thoroughly with water

*Stop use and ask a doctor if irritation or rash appears and lasts 72

hours

*Keep out of the reach of children.If swallowed, get medical help or

contact a Poison Control Center right away.

Do not use

/

*When using this product do not use in or near the eyes
In case of contact, rinse eyes thoroughly with water

*Stop use and ask a doctor if irritation or rash appears and lasts 72 hours

KEEP OUT OF REACH OF CHILDREN

*Keep out of the reach of children.If swallowed, get medical help or contact a Poison Control Center right away.

Directions

·Wet hands thoroughly with product and allow to dry
·Discard wipes in trash receptacle after use-Do not flush
·Children under 6yrsofage should be supervised if using this product

Other information

1.Filp open dispensing cap and remove seal
2.Pull first wipe at center of roll through small opening in lid
3.For best results, dispense remaining wipe satan angle
4.When finished, close lid cap to retain moisture

Package Label - Principal Display Panel

79683-005-01 60 CLOTH in 1 BAG

79683-005-02 90 CLOTH in 1 DRUM

79683-005-03 160 CLOTH in 1 DRUM